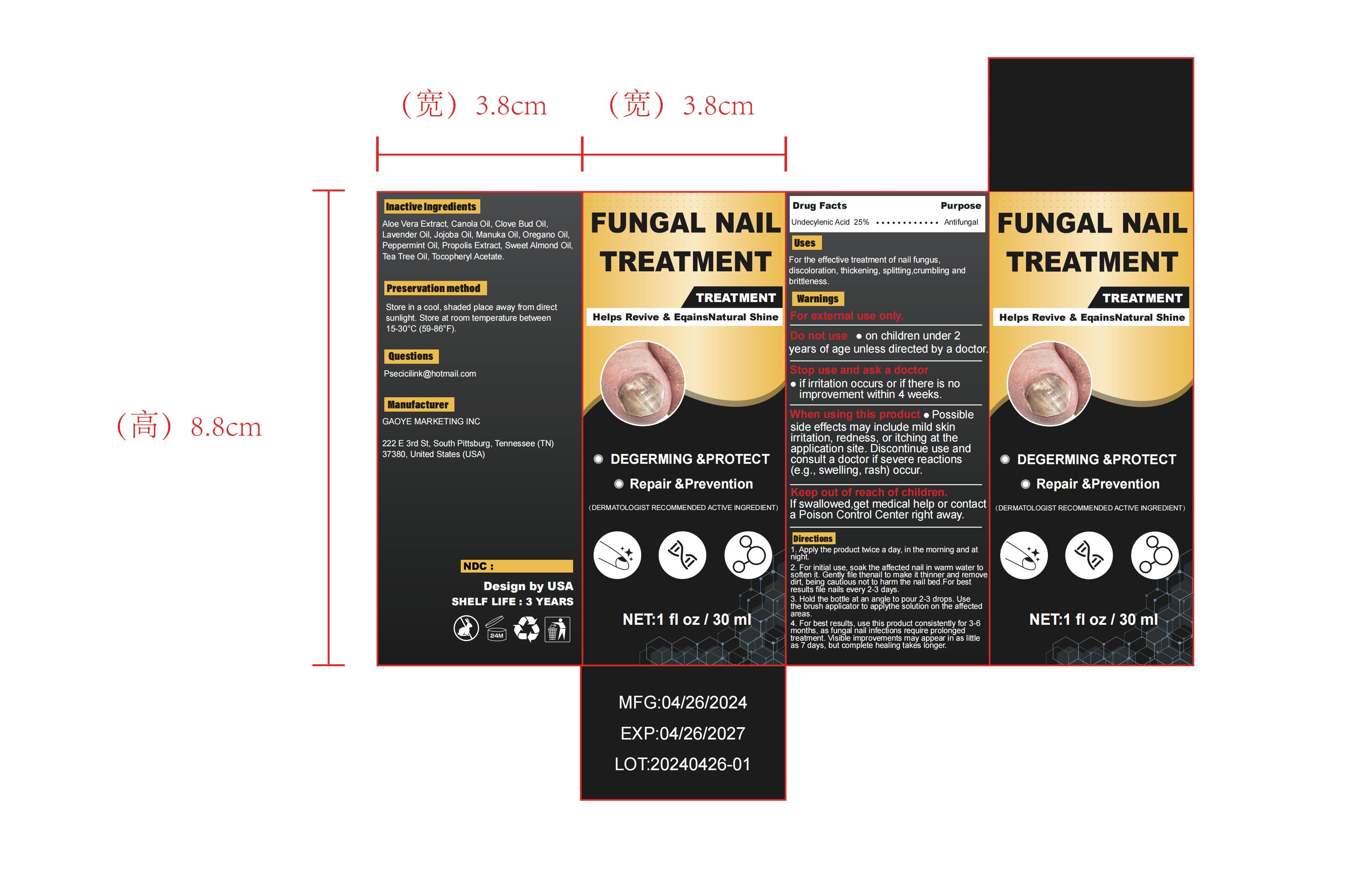 DRUG LABEL: FUNGAL NAIL TREATMENT
NDC: 85308-003 | Form: LIQUID
Manufacturer: Gaoye Marketing Inc
Category: otc | Type: HUMAN OTC DRUG LABEL
Date: 20250411

ACTIVE INGREDIENTS: UNDECYLENIC ACID 25 g/100 mL
INACTIVE INGREDIENTS: PROPOLIS WAX; ALOE VERA LEAF; LAVENDER OIL; JOJOBA OIL; MANUKA OIL; PEPPERMINT OIL; TEA TREE OIL; OREGANO LEAF OIL; .ALPHA.-TOCOPHEROL ACETATE; CANOLA OIL; ALMOND OIL; CLOVE OIL

85308-003

Active Ingredient

Undecylenic Acid 25%

Purpose

Antifungal

Use

For the effective treatment of nail fungus,discoloration, thickening, splitting,crumbling and brittleness.

Warnings

For external use only.
Do not use● on children under 2 years of age unless directed by a doctor.
Stop use and ask a doctor
●if irritation occurs or if there is no improvement within 4 weeks.
When using this product●Possible
side effects may include mild skin irritation, redness, or itching at the application site. Discontinue use and consult a doctor if severe reactions(e.g., swelling, rash) occur.
Keep out of reach of children.
If swallowed,get medical help or contacta Poison Control Center right away.

Do not use

on children under 2 years of age unless directed by a doctor.

When Using

When using this product●Possible
side effects may include mild skin irritation, redness, or itching at the application site. Discontinue use and consult a doctor if severe reactions(e.g., swelling, rash) occur.

Stop Use

Stop use and ask a doctor
●if irritation occurs or if there is no improvement within 4 weeks.

Ask Doctor

Stop use and ask a doctor
●if irritation occurs or if there is no improvement within 4 weeks.

Keep Oot Of Reach Of Children

Keep out of reach of children.
If swallowed,get medical help or contacta Poison Control Center right away.

Directions

1. Apply the product twice a day, in the morning and at night.
2.For initial use, soak the affected nail in warm water to soften it. Gently file thenail to make it thinner and remove dirt, being cautious not to harm the nail bed.For best results file nails every 2-3 days.
3. Hold the bottle at an angle to pour 2-3 drops.Use the brush applicator to applythe solution on the affected areas.
4. For best results, use this product consistenthy for 3-6 months, as fungal nail infections require prolonged treatment. Visible improvements may appear in as little as 7 days, but complete healing takes longer.

Other information

Preservation method
Store in a cool, shaded place away from direct sunlight. Store at room temperature between15-30°C(59-86°F).

Inactive ingredients

Aloe Vera Extract, Canola Oil, Clove Bud Oil,Lavender Oil, Jojoba Oil, Manuka Oil, Oregano Oil,Peppermint Oil, Propolis Extract, Sweet Almond Oil.Tea Tree Oil, Tocopheryl Acetate.

Questions

Psecicilink@hotmail.com